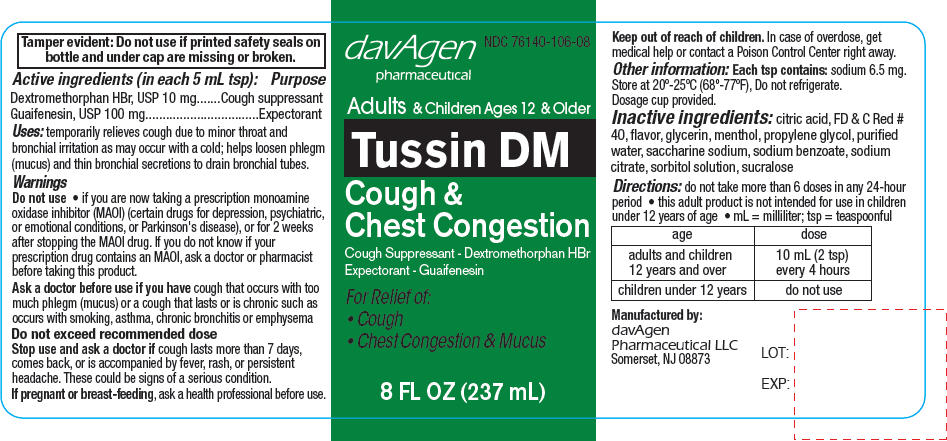 DRUG LABEL: Tussin DM
NDC: 76140-106 | Form: LIQUID
Manufacturer: davAgen Pharmaceutical, LLC
Category: otc | Type: HUMAN OTC DRUG LABEL
Date: 20131230

ACTIVE INGREDIENTS: Dextromethorphan Hydrobromide 10 mg/5 mL; Guaifenesin 100 mg/5 mL
INACTIVE INGREDIENTS: Sodium Benzoate; Citric Acid Monohydrate; Sorbitol; Saccharin Sodium; Sucralose; FD&C Red No. 40; Propylene Glycol; Glycerin; Sodium Citrate; Menthol; Water

Tussin DM

ACTIVE INGREDIENT

Active ingredients (in each 5 mL tsp): | Purpose
Dextromethorphan HBr, USP 10 mg | Cough suppressant
Guaifenesin, USP 100 mg | Expectorant

Uses

temporarily relieves cough due to minor throat and bronchial irritation as may occur with a cold; helps loosen phlegm (mucus) and thin bronchial secretions to drain bronchial tubes.

Warnings

Do not use

- if you are now taking a prescription monoamine oxidase inhibitor (MAOI) (certain drugs for depression, psychiatric, or emotional conditions, or Parkinson's disease), or for 2 weeks after stopping the MAOI drug. If you do not know if your prescription drug contains an MAOI, ask a doctor or pharmacist before taking this product.

Ask a doctor before use if you have cough that occurs with too much phlegm (mucus) or a cough that lasts or is chronic such as occurs with smoking, asthma, chronic bronchitis or emphysema

Do not exceed recommended dose

Stop use and ask a doctor if cough lasts more than 7 days, comes back, or is accompanied by fever, rash, or persistent headache. These could be signs of a serious condition.

PREGNANCY OR BREAST FEEDING

If pregnant or breast-feeding, ask a health professional before use.

Keep out of reach of children. In case of overdose, get medical help or contact a Poison Control Center right away.

Other information

Each tsp contains: sodium 6.5 mg. Store at 20°-25°C (68°-77°F), Do not refrigerate.

Dosage cup provided.

Inactive ingredients

citric acid, FD & C Red # 40, flavor, glycerin, menthol, propylene glycol, purified water, saccharine sodium, sodium benzoate, sodium citrate, sorbitol solution, sucralose

Directions

do not take more than 6 doses in any 24-hour period

- this adult product is not intended for use in children under 12 years of age
- mL = milliliter; tsp = teaspoonful

age | dose
adults and children 12 years and over | 10 mL (2 tsp) every 4 hours
children under 12 years | do not use

Manufactured by:
davAgen
Pharmaceutical LLC
Somerset, NJ 08873

PRINCIPAL DISPLAY PANEL - 237 mL Bottle Label

davAgen
pharmaceutical

NDC 76140-106-08

Adults & Children Ages 12 & Older

Tussin DM
Cough &
Chest Congestion

Cough Suppressant - Dextromethorphan HBr
Expectorant - Guaifenesin

For Relief of:

- Cough
- Chest Congestion & Mucus

8 FL OZ (237 mL)